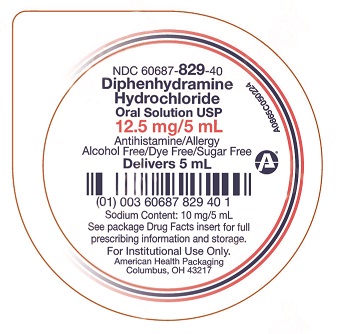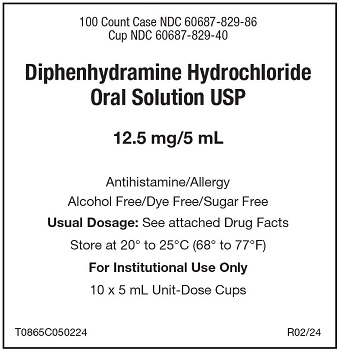 DRUG LABEL: Diphenhydramine HCl
NDC: 60687-829 | Form: SOLUTION
Manufacturer: American Health Packaging
Category: otc | Type: HUMAN OTC DRUG LABEL
Date: 20240804

ACTIVE INGREDIENTS: DIPHENHYDRAMINE HYDROCHLORIDE 12.5 mg/5 mL
INACTIVE INGREDIENTS: ANHYDROUS CITRIC ACID; GLYCERIN; WATER; SACCHARIN SODIUM; SODIUM BENZOATE; CARBOXYMETHYLCELLULOSE SODIUM, UNSPECIFIED; SODIUM CITRATE, UNSPECIFIED FORM; SORBITOL

Diphenhydramine Hydrochloride Oral Solution USP
Drug Facts

Active ingredient (in each 5 mL)

Diphenhydramine HCl 12.5 mg

Purpose

Antihistamine

Uses

- temporarily relieves these symptoms due to hay fever or other upper respiratory allergies:
  - runny nose
  - sneezing
  - itchy, watery eyes
  - itching of the nose or throat

Warnings

Do not use

- to make a child sleepy
- with any other product containing diphenhydramine, even one used on skin

Ask a doctor before use if the child has

- a breathing problem such as chronic bronchitis
- glaucoma

Ask a doctor or pharmacist

before use if the child is taking sedatives or tranquilizers

When using this product

- marked drowsiness may occur
- sedatives and tranquilizers may increase drowsiness
- excitability may occur, especially in children

Keep out of reach of children.

In case of overdose, get medical help or contact a Poison Control Center right away. (1-800-222-1222)

Directions:

- find right dose on chart below
- mL = milliliter
- take every 4 to 6 hours, or as directed by a doctor
- do not take more than 6 doses in 24 hours

Age (yr) | Dose (mL)
children under 2 years | do not use
children 2 to 5 years | do not use unless directed by a doctor
children 6 to 11 years | 5 mL to 10 mL

Other information

- each 5 mL contains: sodium 10 mg
- store between 20-25°C (68-77°F). Protect from light. Store in outer carton until contents used.

Diphenhydramine HCl Oral Solution, USP is a clear, cherry flavored liquid supplied in the following:
5 mL unit dose cups: 100 cups (10 x 10) NDC 60687-829-86

Inactive ingredients:

citric acid anhydrous, glycerin, flavoring, purified water, saccharin sodium, sodium benzoate, sodium carboxymethylcellulose, sodium citrate, sorbitol.

Questions or comments?

Call 1-800-845-8210

DO NOT USE IF SEAL IS BROKEN.

Distributed by:
American Health Packaging
Columbus, OH 43217

R02/24

Principal Display Panel - Label

100 Count Case NDC 60687-829-86
Cup NDC 60687-829-40

Diphenhydramine Hydrochloride
Oral Solution USP

12.5 mg/5 mL

Antihistamine/Allergy
Alcohol Free/Dye Free/Sugar Free

Usual Dosage: See attached Drug Facts

Store at 20° to 25°C (68° to 77°F)

For Institutional Use Only

10 x 5 mL Unit-Dose Cups

T0865C050224 R02/24

Principal Display Panel – Cup – 12.5 mg/5 mL

NDC 60687- 829-40

Diphenhydramine
Hydrochloride
Oral Solution USP

12.5 mg/5 mL

Antihistamine/Allergy
Alcohol Free/Dye Free/Sugar Free

Delivers 5 mL

Sodium Content: 10 mg/5 ml

See package Drug Facts insert for full
prescribing information and storage.

For Institutional Use Only.

American Health Packaging
Columbus, OH 43217

A0865C050224